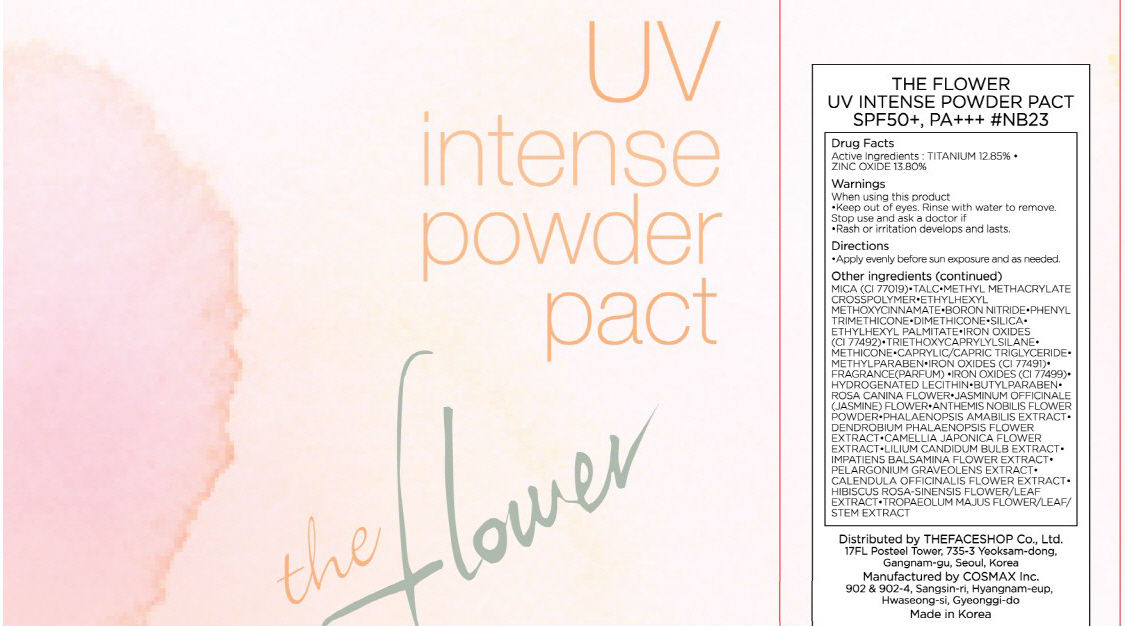 DRUG LABEL: THE FLOWER UV INTENSE PACT
NDC: 51523-024 | Form: POWDER
Manufacturer: THEFACESHOP CO., LTD.
Category: otc | Type: HUMAN OTC DRUG LABEL
Date: 20100714

ACTIVE INGREDIENTS: ZINC OXIDE 1.65 g/12 g; TITANIUM DIOXIDE 1.54 g/12 g

Drug Facts

Active Ingredients: ZINC OXIDE, TITANIUM DIOXIDE

Inactive Ingredients:
MICA(CI 77019), TALC, METHYL METHACRYLATE CROSSPOLYMER, ETHYLHEXYL METHOXYCINNAMATE, BORON NITRIDE, PHENYL TRIMETHICONE, DIMETHICONE, SILICA,
ETHYLHEXYL PALMITATE, IRON OXIDES(CI 77492), TRIETHOXYCAPRYLYLSILANE, METHICONE, CAPRYLIC/CAPRIC TRIGLYCERIDE, METHYLPARABEN, IRON OXIDES(CI 77491),
FRAGRANCE, IRON OXIDES(CI 77499), HYDROGENATED LECITHIN, BUTYLPARABEN, ROSA CANINA FLOWER, JASMINUM OFFICINALE (JASMINE) FLOWER,
ANTHEMIS NOBILIS FLOWER POWDER, PHALAENOPSIS AMABILIS EXTRACT, DENDROBIUM PHALAENOPSIS FLOWER EXTRACT, CAMELLIA JAPONICA FLOWER EXTRACT,
LILIUM CANDIDUM BULB EXTRACT, IMPATIENS BALSAMINA FLOWER EXTRACT, PELARGONIUM GRAVEOLENS EXTRACT, CALENDULA OFFICINALIS FLOWER EXTRACT,
HIBISCUS ROSA-SINENSIS FLOWER/LEAF EXTRACT, TROPAEOLUM MAJUS FLOWER/LEAF/STEM EXTRACT

Warnings:
When using this product
Keep out of eyes. Rinse with water to remove.
Stop use and ask a doctor if
Rash or irritation develops and lasts.
Directions:
Apply evenly before sun exposure and as needed.